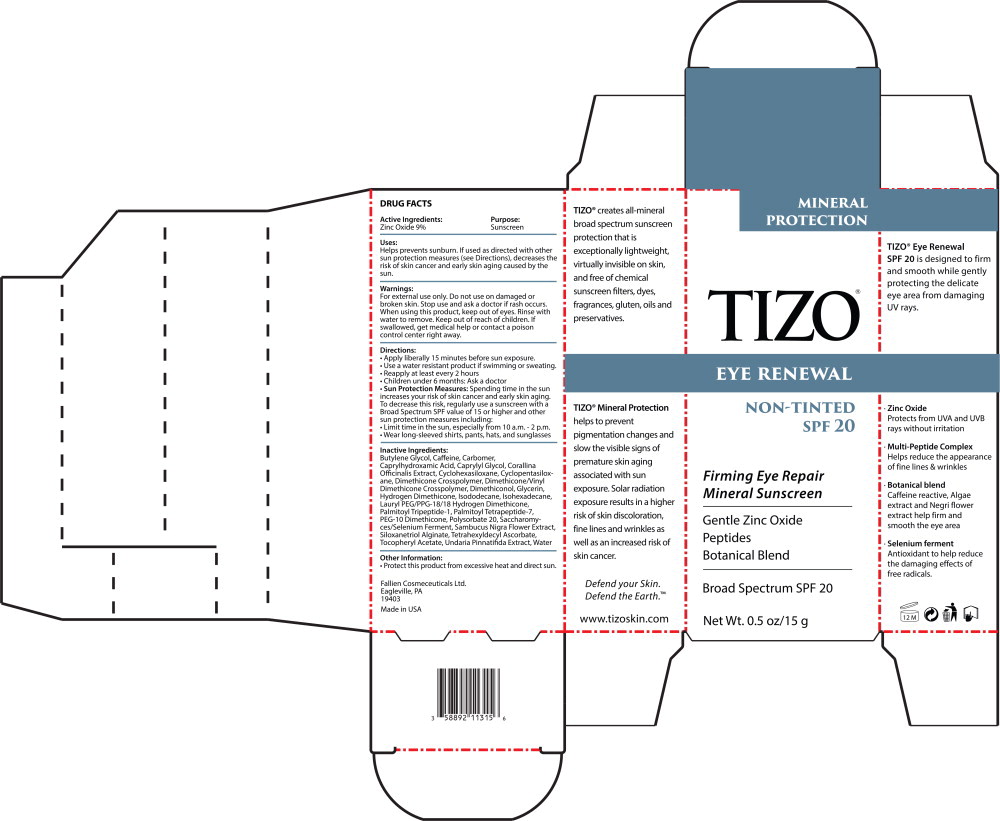 DRUG LABEL: TiZO Eye Renewal SPF 20 (Non-Tinted)
NDC: 58892-113 | Form: CREAM
Manufacturer: Fallien Cosmeceuticals, LTD
Category: otc | Type: HUMAN OTC DRUG LABEL
Date: 20241018

ACTIVE INGREDIENTS: ZINC OXIDE 90 mg/1 g
INACTIVE INGREDIENTS: BUTYLENE GLYCOL; CAFFEINE; CARBOMER HOMOPOLYMER, UNSPECIFIED TYPE; CAPRYLHYDROXAMIC ACID; CAPRYLYL GLYCOL; CORALLINA OFFICINALIS; CYCLOMETHICONE 6; CYCLOMETHICONE 5; DIMETHICONE CROSSPOLYMER (450000 MPA.S AT 12% IN CYCLOPENTASILOXANE); DIMETHICONE/VINYL DIMETHICONE CROSSPOLYMER (SOFT PARTICLE); DIMETHICONOL (2000 CST); GLYCERIN; HYDROGEN DIMETHICONE (20 CST); ISODODECANE; ISOHEXADECANE; LAURYL PEG/PPG-18/18 METHICONE; PALMITOYL TRIPEPTIDE-1; PALMITOYL TETRAPEPTIDE-7; PEG-10 DIMETHICONE (600 CST); POLYSORBATE 20; SACCHAROMYCES CEREVISIAE; SAMBUCUS NIGRA FLOWER; SILANETRIOL; TETRAHEXYLDECYL ASCORBATE; .ALPHA.-TOCOPHEROL ACETATE; UNDARIA PINNATIFIDA; WATER

Active Ingredients:

Zinc Oxide 9%

Purpose:

Sunscreen

Uses:

Helps prevents sunburn. If used as directed with other sun protection measures (see Directions), decreases the risk of skin cancer and early skin aging caused by the sun.

Warnings:

For external use only. Do not use on damaged or broken skin. Stop use and ask a doctor if rash occurs. When using this product, keep out of eyes. Rinse with water to remove. Keep out of reach of children. If swallowed, get medical help or contact a poison control center right away.

Directions:

- Apply liberally 15 minutes before sun exposure.
- Use a water resistant product if swimming or sweating.
- Reapply at least every 2 hours
- Children under 6 months: Ask a doctor
- Sun Protection Measures:Spending time in the sun increases your risk of skin cancer and early skin aging. To decrease this risk, regularly use a sunscreen with a Broad Spectrum SPF value of 15 or higher and other sun protection measures including:
  - Limit time in the sun, especially from 10 a.m.-2 p.m.
  - Wear long-sleeved shirts, pants, hats, and sunglasses

Inactive Ingredients:

Butylene Glycol, Caffeine, Carbomer, Caprylhydroxamic Acid, Caprylyl Glycol, Corallina Officinalis Extract, Cyclohexasiloxane, Cyclopentasiloxane, Dimethicone Crosspolymer, Dimethicone/Vinyl Dimethicone Crosspolymer, Dimethiconol, Glycerin, Hydrogen Dimethicone, Isododecane, Isohexadecane, Lauryl PEG/PPG-18/18 Hydrogen Dimethicone,PaImitoyI Tripeptide-1, PaImitoyl Tetrapeptide-7, PEG-10 Dimethicone, Polysorbate 20, Saccharomy- ces/Selenium Ferment, Sambucus Nigra Flower Extract, Siloxanetriol Alginate, Tetrahexyldecyl Ascorbate, Tocopheryl Acetate, Undaria Pinnatifida Extract, Water

Other Information:

- Protect this product from excessive heat and direct sun.

Keep out of reach of children.

Principal Display Panel - 100 g Carton Label

MINERAL
PROTECTION

TIZO®

EYE RENEWAL

NON-TINTED
SPF 20

Firming Eye Repair

Mineral Sunscreen

Gentle Zinc Oxide

Peptides

Botanical Blend

Broad Spectrum SPF 20

Net Wt. 0.5 oz/15 g